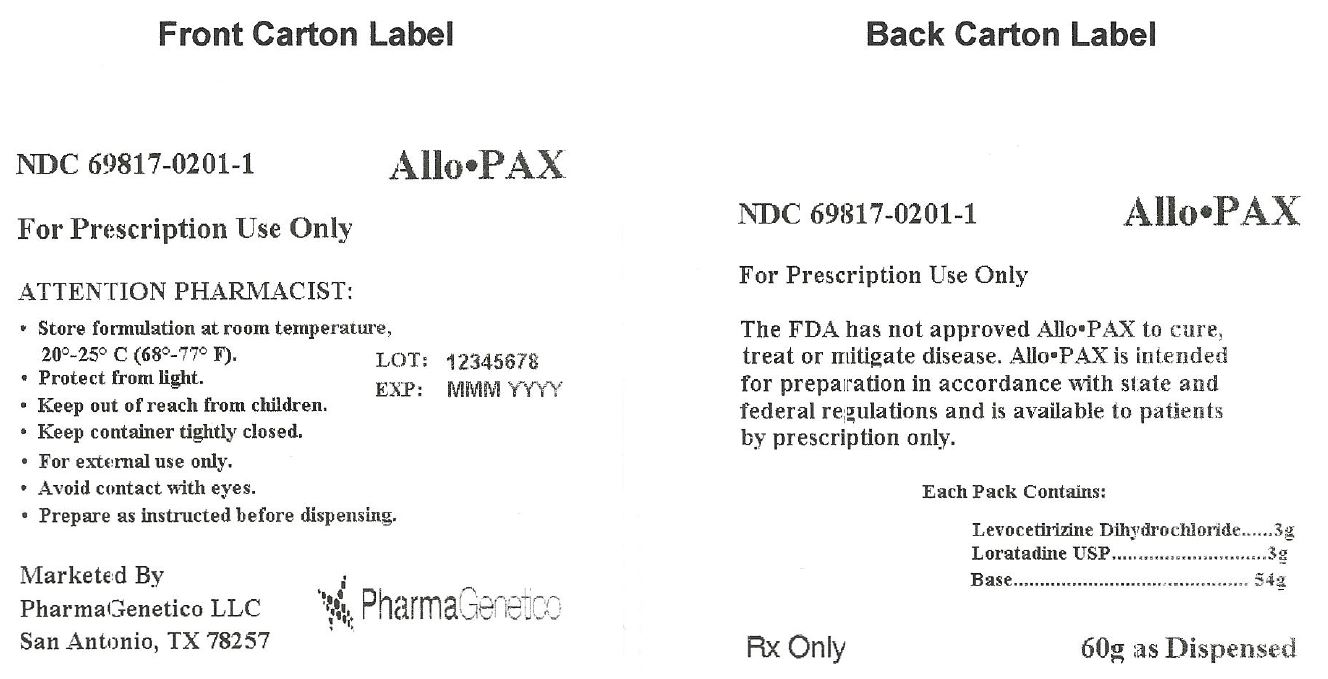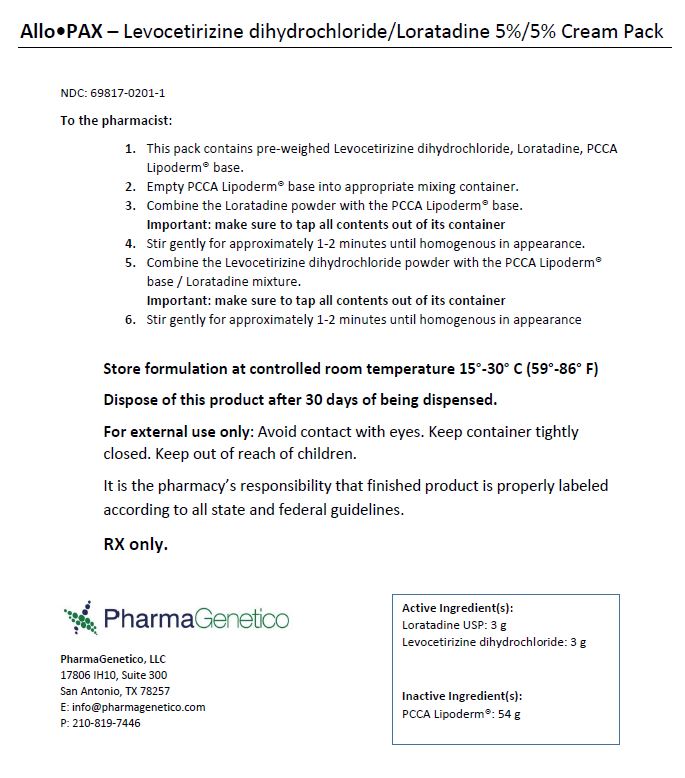 DRUG LABEL: AlloPAX
NDC: 69817-0201 | Form: KIT | Route: TRANSDERMAL
Manufacturer: PharmaGenetico LLC
Category: prescription | Type: HUMAN PRESCRIPTION DRUG LABEL
Date: 20170725

ACTIVE INGREDIENTS: LORATADINE 3 g/3 g; LEVOCETIRIZINE DIHYDROCHLORIDE 3 g/3 g
INACTIVE INGREDIENTS: WATER; ISOPROPYL MYRISTATE; LECITHIN, SOYBEAN; CETOSTEARYL ALCOHOL; WHEAT GERM OIL; CETYL ALCOHOL; STEARYL ALCOHOL; POLYOXYL 20 CETOSTEARYL ETHER; GLYCERIN; DIMETHICONE; C13-14 ISOPARAFFIN; LAURETH-7; XANTHAN GUM; MAGNESIUM ALUMINUM SILICATE; EDETATE DISODIUM; BUTYLATED HYDROXYTOLUENE; PHENOXYETHANOL; METHYLISOTHIAZOLINONE; METHYLCHLOROISOTHIAZOLINONE; POLYACRYLAMIDE (10000 MW); MEDIUM-CHAIN TRIGLYCERIDES

AlloPAX

DESCRIPTION

Each Allo•PAX provides 3 grams of Levocetirizine dihydrochloride, 3 grams Loratadine USP, and 54 grams of Base. The resulting mixture is intended for transdermal use.

For Prescription Use Only

Distributed by:

PharmaGenetico LLC

San Antonio, TX 78257